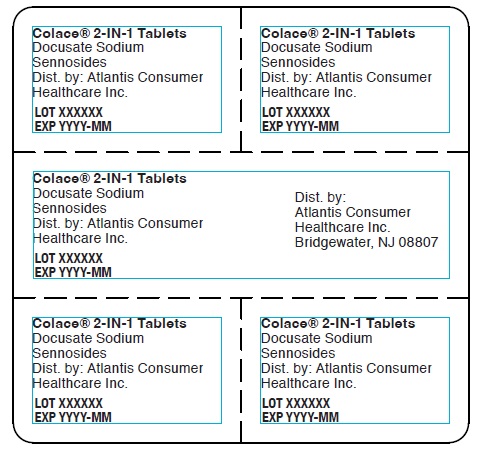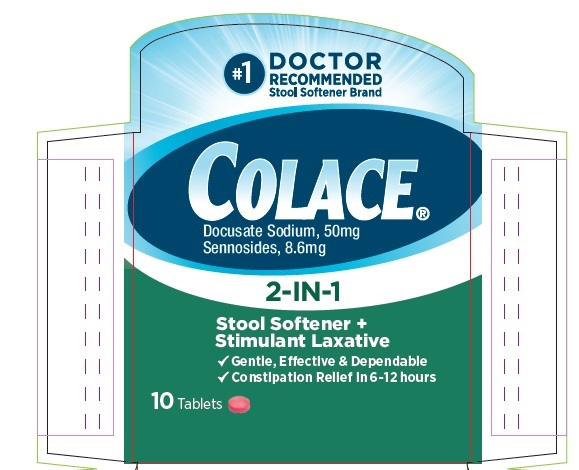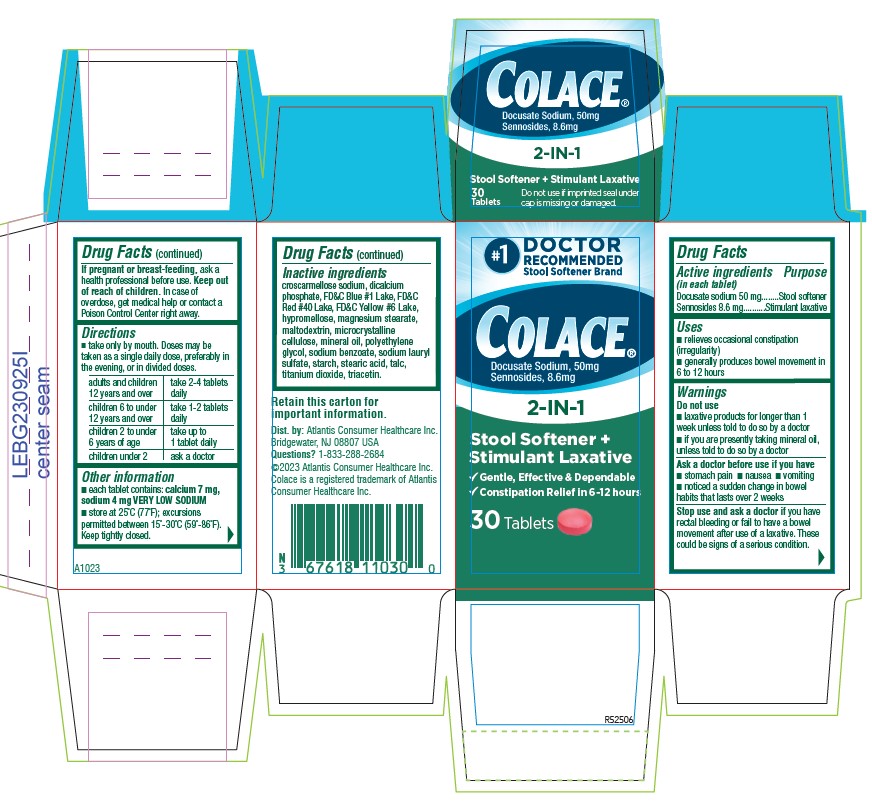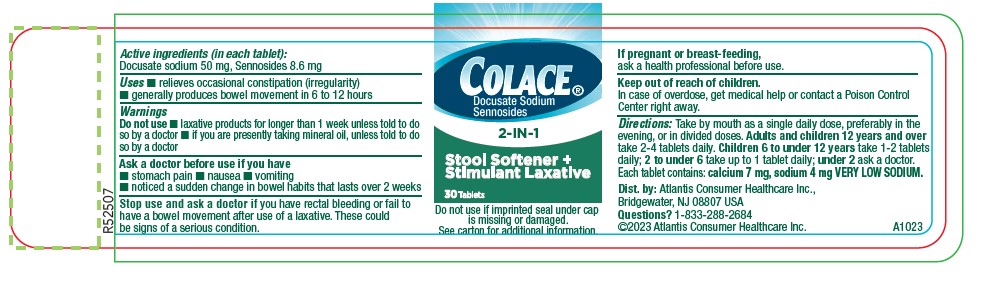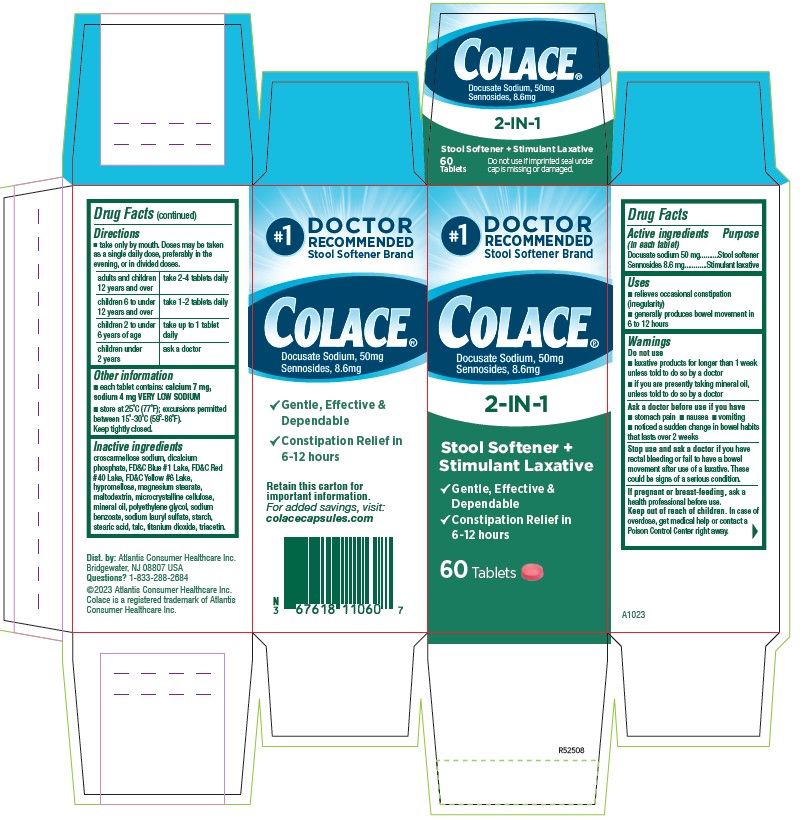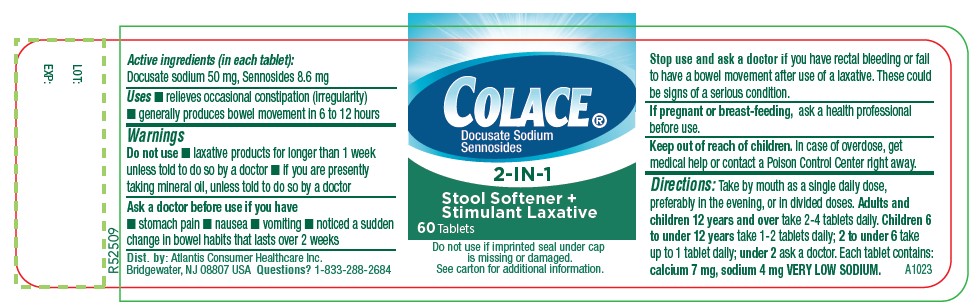 DRUG LABEL: Colace
NDC: 67618-110 | Form: TABLET, FILM COATED
Manufacturer: Atlantis Consumer Healthcare, Inc.
Category: otc | Type: HUMAN OTC DRUG LABEL
Date: 20250417

ACTIVE INGREDIENTS: DOCUSATE SODIUM 50 mg/1 1; SENNOSIDES 8.6 mg/1 1
INACTIVE INGREDIENTS: MICROCRYSTALLINE CELLULOSE 102; MINERAL OIL; POLYETHYLENE GLYCOL, UNSPECIFIED; SODIUM BENZOATE; SODIUM LAURYL SULFATE; STARCH, CORN; STEARIC ACID; TALC; TITANIUM DIOXIDE; TRIACETIN; CROSCARMELLOSE SODIUM; ANHYDROUS DIBASIC CALCIUM PHOSPHATE; FD&C BLUE NO. 1; FD&C RED NO. 40; FD&C YELLOW NO. 6; HYPROMELLOSE, UNSPECIFIED; MAGNESIUM STEARATE; MALTODEXTRIN

Colace

Drug Facts

Active ingredient | Purpose
Docusate sodium 50 mg | Stool softener
Sennosides 8.6 mg | Stimulant laxative

Uses

- relieves occasional constipation (irregularity)
- generally produces bowel movement in 6 to 12 hours

Warnings

Do not use

- laxative products for longer than 1 week unless told to do so by a doctor
- if you are presently taking mineral oil, unless told to do so by a doctor

Ask a doctor before use if you have

- stomach pain
- nausea
- vomiting
- noticed a sudden change in bowel habits that lasts over 2 weeks

Stop use and ask a doctor ifyou have rectal bleeding or fail to have a bowel movement after use of a laxative. These could be signs of a serious condition.

PREGNANCY OR BREAST FEEDING

If pregnant or breast-feeding,ask a health professional before use.

Keep out of reach of children.
In case of overdose, get medical help or contact a Poison Control Center right away.

Directions

- Take only by mouth. Doses may be taken as a single daily dose, preferably in the evening, or in divided doses.

adults and children 12 years and over | take 2-4 tablets daily
children 6 to under 12 years of age | take 1-2 tablets daily
children 2 to under 6 years of age | take up to 1 tablet daily
children under 2 | ask a doctor

Other information

- each tablet contains: calcium 7 mg, sodium 4 mg VERY LOW SODIUM
- store at 25°C (77°F); excursions permitted between 15°-30°C (59°-86°F).
  Keep tightly closed..

Inactive ingredients

croscarmellose sodium, dicalcium phosphate, FD&C Blue #1 Lake, FD&C Red #40 Lake, FD&C Yellow #6 Lake, hypromellose, magnesium stearate, maltodextrin, microcrystalline cellulose, mineral oil, polyethylene glycol, sodium benzoate, sodium lauryl sulfate, starch, stearic acid, talc, titanium dioxide, triacetin.

Dist. by: Atlantis Consumer Healthcare inc.
Bridgewater, NJ 08801 USA
Questions? 1-833-286-2684
©2023 Atlantis Consumer Healthcare inc.
Colace is a registered trademark of Atlantis
Consumer Healthcare Inc.
A1023
R52504

PACKAGE LABEL.PRINCIPAL DISPLAY PANEL

#1
DOCTOR
RECOMMENDED
Stool Softener Brand
Colace®
Docusate Sodium, 50 mg
Sennosides 8.6 mg
2-IN-1
Stool Softener +
Stimulant Laxative
√ Gentle, Effective, & Dependable
√ Constipation Relief in 6 `12 hours
10Tablets

Colace® 2-IN-1 Tablets
Docusate Sodium
Sennosides
Dist. by: Atlantis Consumer
Healthcare Inc.
LOT XXXXXX
EXP YYYY-MM

#1
DOCTOR
RECOMMENDED
Stool Softener Brand
Colace®
Docusate Sodium, 50 mg
Sennosides 8.6 mg
2-IN-1
Stool Softener +
Stimulant Laxative
√ Gentle, Effective, & Dependable
√ Constipation Relief in 6 `12 hours
30Tablets
Retain this carton for
Important information
Dist. by: Atlantis Consumer Healthcare inc.
Bridgewater, NJ 08801 USA
Questions?1-833-286-2684
©2023 Atlantis Consumer Healthcare inc.
Colace is a registered trademark of Atlantis
Consumer Healthcare Inc.
A1023
R52506

Colace®
Docusate Sodium
Sennosides
2-IN-1
Stool Softener +
Stimulant Laxative
30Tablets
Do not use if imprinted seal under cap
is missing or damaged.
See carton for additional information
Dist. by: Atlantis Consumer Healthcare inc.
Bridgewater, NJ 08801 USA
Questions?1-833-286-2684
©2023 Atlantis Consumer Healthcare inc.
Colace is a registered trademark of Atlantis
Consumer Healthcare Inc.
A1023
R52507

#1
DOCTOR
RECOMMENDED
Stool Softener Brand
Colace®
Docusate Sodium, 50 mg
Sennosides 8.6 mg
2-IN-1
Stool Softener +
Stimulant Laxative
√ Gentle, Effective, & Dependable
√ Constipation Relief in 6 `12 hours
Retain this carton for
Important information
For added savings, visit:
colacecapsules.com
Dist. by: Atlantis Consumer Healthcare inc.
Bridgewater, NJ 08801 USA
Questions? 1-833-286-2684
©2023 Atlantis Consumer Healthcare inc.
Colace is a registered trademark of Atlantis
Consumer Healthcare Inc.
A1023
R52508
60Tablets
A1023
R52507

Colace®
Docusate Sodium
Sennosides
2-IN-1
Stool Softener +
Stimulant Laxative
60Tablets
Do not use if imprinted seal under cap
is missing or damaged.
See carton for additional information
Dist. by: Atlantis Consumer Healthcare inc.
Bridgewater, NJ 08801 USA
Questions?1-833-286-2684
©2023 Atlantis Consumer Healthcare inc.
Colace is a registered trademark of Atlantis
Consumer Healthcare Inc.
LOT:
EXP:
A1023
R52509